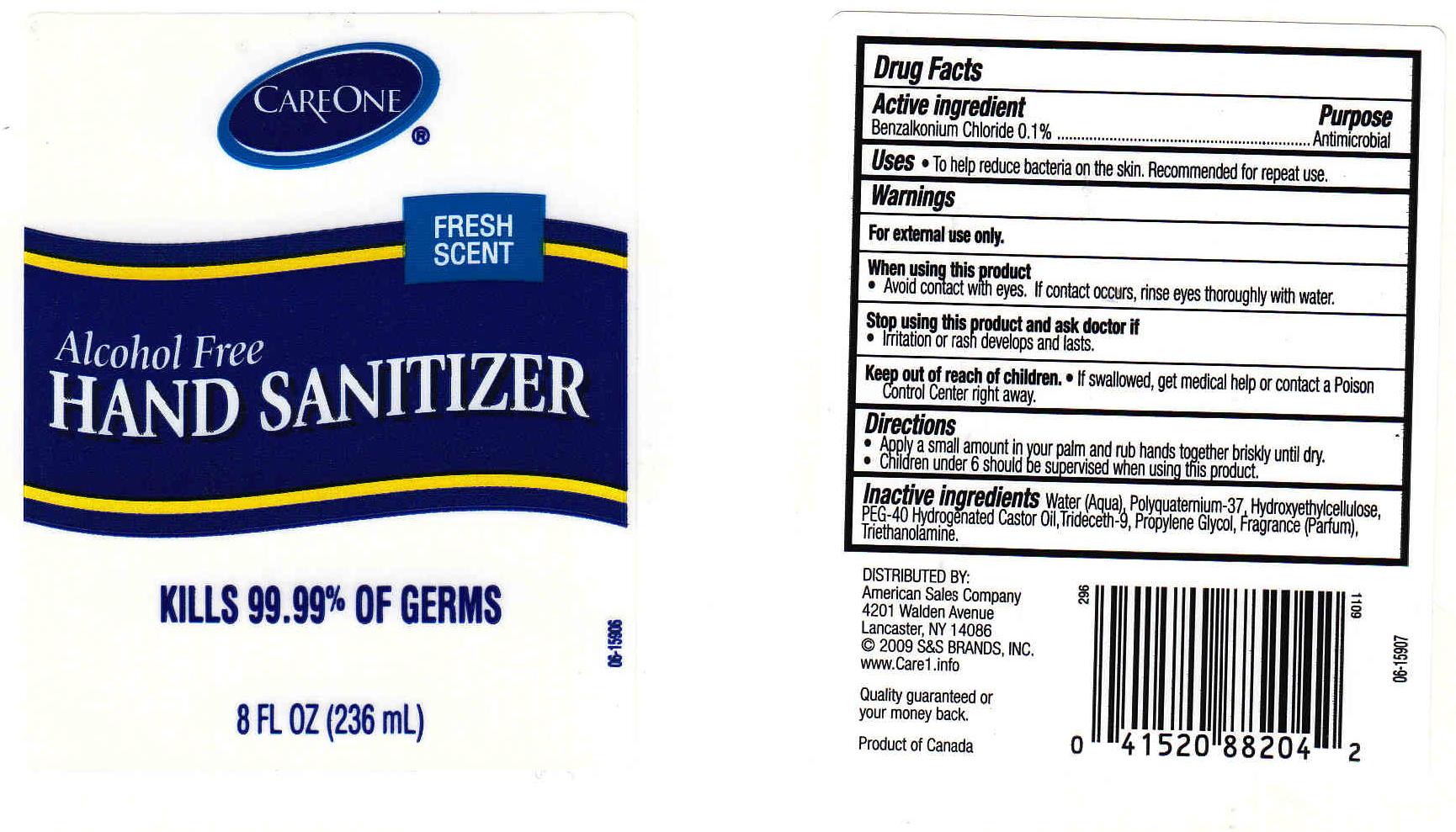 DRUG LABEL: HAND SANITIZER
NDC: 41520-280 | Form: GEL
Manufacturer: AMERICAN SALES COMPANY
Category: otc | Type: HUMAN OTC DRUG LABEL
Date: 20111006

ACTIVE INGREDIENTS: BENZALKONIUM CHLORIDE 0.1 mL/100 mL
INACTIVE INGREDIENTS: WATER; HYPROMELLOSES; POLYOXYL 40 HYDROGENATED CASTOR OIL; TRIDECETH-9; PROPYLENE GLYCOL; TROLAMINE

DRUG FACTS

ACTIVE INGREDIENT

BENZALKONIUM CHLORIDE 0.1%

PURPOSE

ANTIMICROBIAL

USES

TO HELP REDUCE BACTERIA ON THE SKIN. RECOMMENDED FOR REPEAT USE.

WARNINGS

FOR EXTERNAL USE ONLY.

WHEN USING THIS PRODUCT

AVOID CONTACT WITH EYES. IF CONTACT OCCURS, RINSE EYES THOROUGHLY WITH WATER.

STOP USING THIS PRODUCT AND ASK DOCTOR IF

IRRITATION OR RASH DEVELOPS AND LASTS.

KEEP OUT OF REACH OF CHILDREN

IF SWALLOWED, GET MEDICAL HELP OR CONTACT A POISON CONTROL CENTER RIGHT AWAY.

DIRECTIONS

- APPLY A SMALL AMOUNT IN YOUR PALM AND RUB HANDS TOGETHER BRISKLY UNTIL DRY.
- CHILDREN UNDER 6 SHOULD BE SUPERVISED WHEN USING THIS PRODUCT.

INACTIVE INGREDIENTS

WATER, POLYQUATERNIUM-37, HYDROXYETHYLCELLULOSE, PEG-40 HYDROGENATED CASTOR OIL, TRIDECETH-9, PROPYLENE GLYCOL, FRAGRANCE, TRIETHANOLAMINE.